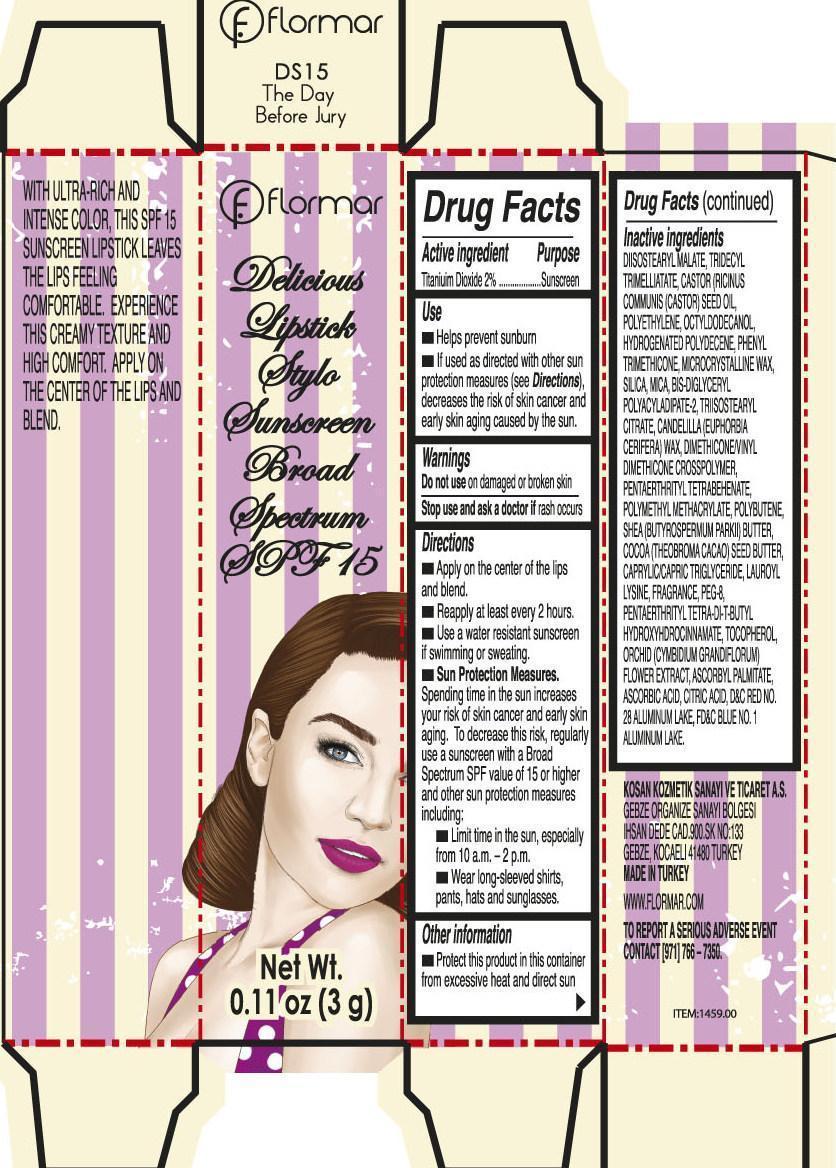 DRUG LABEL: Flormar Delicious Lip Stylo Sunscreen Broad Spectrum SPF 15 DS15 The Day Before Jury
NDC: 61722-240 | Form: STICK
Manufacturer: Kosan Kozmetik Sanayi ve Ticaret A.S.
Category: otc | Type: HUMAN OTC DRUG LABEL
Date: 20191018

ACTIVE INGREDIENTS: TITANIUM DIOXIDE 20 mg/1 g
INACTIVE INGREDIENTS: DIISOSTEARYL MALATE; TRIDECYL TRIMELLITATE; HIGH DENSITY POLYETHYLENE; OCTYLDODECANOL; PHENYL TRIMETHICONE; MICROCRYSTALLINE WAX; SILICON DIOXIDE; MICA; TRIISOSTEARYL CITRATE; MEDIUM-CHAIN TRIGLYCERIDES; LAUROYL LYSINE; POLYETHYLENE GLYCOL 400; PENTAERYTHRITOL TETRAKIS(3-(3,5-DI-TERT-BUTYL-4-HYDROXYPHENYL)PROPIONATE); TOCOPHEROL; ASCORBYL PALMITATE; ASCORBIC ACID; CITRIC ACID MONOHYDRATE

Flormar Delicious Lipstick Stylo Sunscreen Broad Spectrum SPF 15 DS15 The Day Before Jury

Active ingredient

Titanium Dioxide 2%

Purpose

Sunscreen

Use

- Helps prevent sunburn
- If used as directed with other sun protection measures (see Directions), decreases the risk of skin cancer and early skin aging caused by the sun.

Warnings

For external use only

Do not use

on damaged or broken skin

Stop use and ask a doctor if

rash occurs

Directions

- Apply on the center of the lips and blend
- Reapply at least every 2 hours.
- Use a water resistant sunscreen if swimming or sweating.
- Sun Protection Measures. Spending time in the sun increases your risk of skin cancer and early skin aging. To decrease this risk, regularly use a sunscreen with a Broad Spectrum SPF value of 15 or higher and other sun protection measures including:

• Limit time in the sun, especially from 10 a.m. - 2 p.m.

• Wear long-sleeved shirts, pants, hats and sunglasses.

Other information

Protect this product in this container from excessive heat and direct sun

Inactive ingredients

DIISOSTEARYL MALATE, TRIDECYL TRIMELLITATE, CASTOR (RICINUS COMMUNIS (CASTOR) SEED OIL, POLYETHYLENE, OCTYLDODECANOL, HYDROGENATED POLYDECENE, PHENYL TRIMETHICONE, POLYETHYLENE, MICROCRYSTALLINE WAX, SILICA, MICA, BIS-DIGLYCERYL POLYACYLADIPATE-2, TRIISOSTEARYL CITRATE, CANDELILLA (EUPHORBIA CERIFERA) WAX, DIMETHICONE/VINYL DIMETHICONE CROSSPOLYMER, PENTAERTHRITYL TETRABEHENATE, POLYMETHYL METHACRYLATE, POLYBUTENE, SHEA (BUTYROSPERMUM PARKII) BUTTER, COCOA (THEOBROMA COCAO) SEED BUTTER, CAPRYLIC/CAPRIC TRIGLYCERIDE, LAUROYL LYSINE, FRAGRANCE, PEG-8, PENTAERYTHRITYL TETRA-DI-T-BUTYL HYDROXYHYDROCINNAMATE, TOCOPHEROL, ORCHID (CYMBIDIUM GRANDIFLORUM) FLOWER EXTRACT, ASCORBYL PALMITATE, ASCORBIC ACID, CITRIC ACID, D&C RED NO. 28 ALUMINUM LAKE, FD&C BLUE NO. 1 ALUMINUM LAKE.